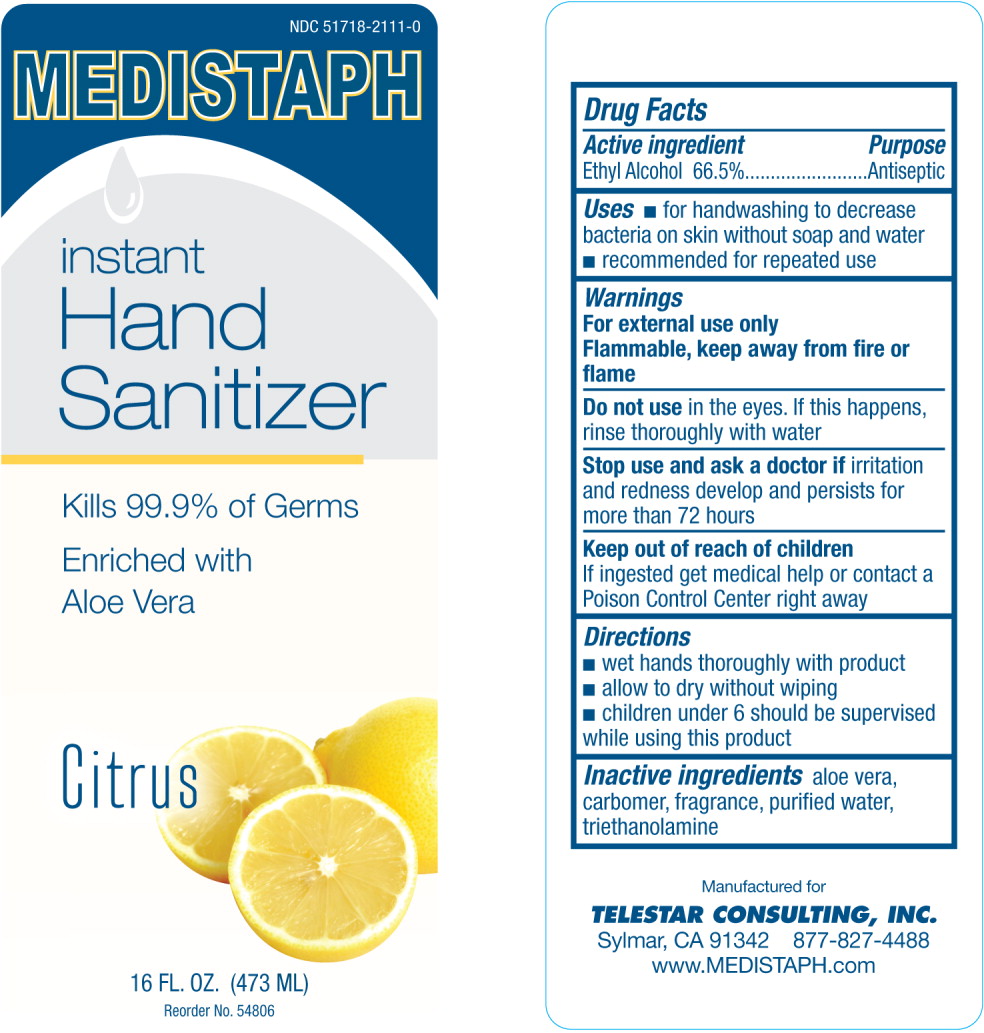 DRUG LABEL: Instant Hand Sanitizer Citrus Scent
NDC: 51718-2111 | Form: GEL
Manufacturer: Telestar Consulting
Category: otc | Type: HUMAN OTC DRUG LABEL
Date: 20100826

ACTIVE INGREDIENTS: alcohol 0.665 g/1 mL
INACTIVE INGREDIENTS: aloe; water; trolamine

Instant Hand Sanitizer Citrus Scent

Drug Facts

Active ingredient

Ethyl Alcohol 66.5%

Purpose

Antiseptic

Uses

- for handwashing to decrease bacteria on skin without soap and water
- recommended for repeated use

Warnings

For external use only

Flammable, keep away from fire or flame

Do not use in the eyes. If this happens, rinse thoroughly with water

Stop use and ask a doctor if irritation and redness develop and persists for more than 72 hours

Keep out of reach of children

If ingested get medical help or contact a Poison Control Center right away

Directions

- wet hands thoroughly with product
- allow to dry without wiping
- children under 6 should be supervised while using this product

Inactive ingredients

aloe vera, carbomer, fragrance, purified water, triethanolamine

Manufactured for
TELESTAR CONSULTING , INC.
Sylmar, CA 91342 877-827-4488
www.MEDISTAPH.com

PRINCIPAL DISPLAY PANEL

NDC 51718-2111-0

MEDISTAPH

instant

Hand

Sanitizer

Kills 99.9% of Germs

Enriched with

Aloe Vera

Citrus

16 FL. OZ. (473 ML)

Reorder No. 54806